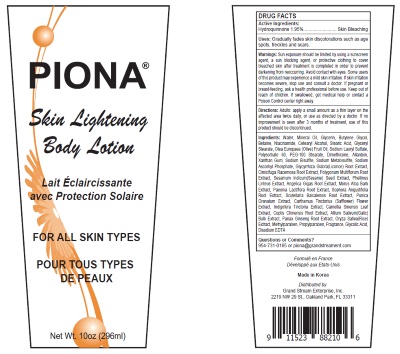 DRUG LABEL: PIONA
NDC: 52927-200 | Form: LOTION
Manufacturer: Grand Stream Enterprise, Inc
Category: otc | Type: HUMAN OTC DRUG LABEL
Date: 20161207

ACTIVE INGREDIENTS: HYDROQUINONE 1.95 1/100 mL
INACTIVE INGREDIENTS: WATER; MINERAL OIL; GLYCERIN; BUTYLENE GLYCOL; BETAINE; NIACINAMIDE; CETOSTEARYL ALCOHOL; GLYCERYL MONOSTEARATE; OLIVE OIL; SODIUM LAURYL SULFATE; POLYSORBATE 60; PEG-100 STEARATE; DIMETHICONE; ALLANTOIN; XANTHAN GUM; SODIUM BISULFATE; SODIUM METABISULFITE; SODIUM ASCORBYL PHOSPHATE; GLYCYRRHIZA GLABRA; BLACK COHOSH; FALLOPIA MULTIFLORA ROOT; SESAME SEED; PHELLINUS LINTEUS MYCELIUM; ANGELICA GIGAS ROOT; MORUS ALBA BARK; PAEONIA LACTIFLORA ROOT; SOPHORA FLAVESCENS ROOT; SCUTELLARIA BAICALENSIS ROOT; PUNICA GRANATUM ROOT BARK; INDIGOFERA TINCTORIA LEAF; GREEN TEA LEAF; COPTIS CHINENSIS ROOT; GARLIC; ASIAN GINSENG; RICE GERM; METHYLPARABEN; PROPYLPARABEN; GLYCOLIC ACID; EDETATE DISODIUM ANHYDROUS; SAFFLOWER; STEARIC ACID

ACTIVE INGREDIENT

HYDROQUINONE 1.95%...............................................Skin Bleaching

INACTIVE INGREDIENT

ALLANTOIN, ANGELICA GIGAS ROOT, ASIAN GINSENG, BETAINE, BLACK COHOSH, BUTYLENE GLYCOL, CETOSTEARYL ALCOHOL, COPTIS CHINENSIS ROOT, DIMETHICONE, EDETATE DISODIUM ANHYDROUS, FALLOPIA MULTIFLORA ROOT, GARLIC, GLYCERIN, GLYCERYL MONOSTEARATE, GLYCOLIC ACID, GLYCYRRHIZA GLABRA, GREEN TEA LEAF, INDIGOFERA TINCTORIA LEAF, METHYLPARABEN, MINERAL OIL, MORUS ALBA BARK, NIACINAMIDE, OLIVE OIL, PAEONIA LACTIFLORA ROOT, PEG-100 STEARATE, PHELLINUS LINTEUS MYCELIUM, POLYSORBATE 60, PROPYLPARABEN, PUNICA GRANATUM ROOT BARK, RICE GERM, SAFFLOWER, SCUTELLARIA BAICALENSIS ROOT, SESAME SEED, SODIUM ASCORBYL PHOSPHATE, SODIUM BISULFATE, SODIUM LAURYL SULFATE, SODIUM METABISULFITE, SOPHORA FLAVESCENS ROOT, STEARIC ACID, WATER, XANTHAN GUM

INDICATIONS & USAGE

Gracually fades skin discolorations such as age spots, freckles and scars.

WARNINGS

Sun exposure should be limited by using a sunscreen agent, a sun blocking agent, or protective clothing to cover bleached skin after treatments completed in order to prevent darkening from reoccurring.
Avoid contact with eyes.
Some users of this product may experience a mild ski, irritation. If ski, irritation becomes severe, stop use and consult a doctor.
If pregnant or breast-feeding, ask a health professional before use.
If swallowed, get medical help or contact a Poison Control center right away.

DOSAGE & ADMINISTRATION

Adults: apply a small amount as a thin layer on the affected area twice daily, or use as drected by a doctor. If no improvement is seen after 3 months of treatment use of this product should be discontinued.

PURPOSE

Skin Bleaching

PIONA Skin Lightening Body Lotion

Questions or Comments? 954-731-0165 or piona@grandstreament.com
Formulated in France
Made in Korea
Distributed by: Grand Stream Enterprise, Inc. 2219 NW 29 St., Oakland Park, FL 33311